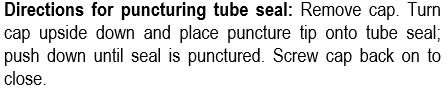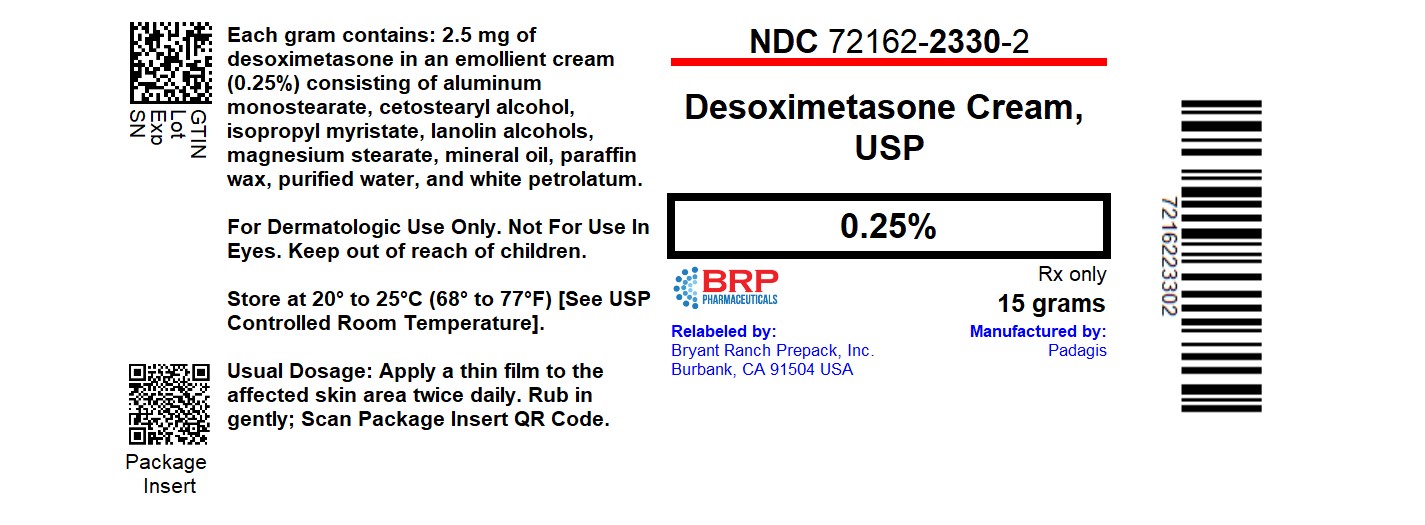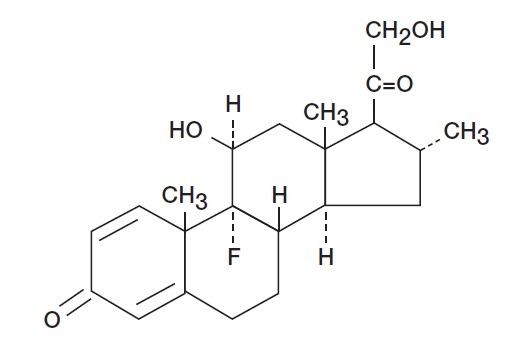 DRUG LABEL: Desoximetasone
NDC: 72162-2330 | Form: CREAM
Manufacturer: Bryant Ranch Prepack
Category: prescription | Type: HUMAN PRESCRIPTION DRUG LABEL
Date: 20250521

ACTIVE INGREDIENTS: DESOXIMETASONE 2.5 mg/1 g
INACTIVE INGREDIENTS: ALUMINUM MONOSTEARATE; CETOSTEARYL ALCOHOL; ISOPROPYL MYRISTATE; LANOLIN ALCOHOLS; MAGNESIUM STEARATE; MINERAL OIL; PARAFFIN; WATER; PETROLATUM

DESOXIMETASONE CREAM USP, 0.25%

For Dermatologic Use Only

Not For Use In Eyes

Rx Only

DESCRIPTION

Desoximetasone Cream USP, 0.25% contains the active synthetic corticosteroid desoximetasone. The topical corticosteroids constitute a class of primarily synthetic steroids used as anti-inflammatory and anti-pruritic agents.

Each gram of Desoximetasone Cream USP, 0.25% contains 2.5 mg of desoximetasone in an emollient cream consisting of aluminum monostearate, cetostearyl alcohol, isopropyl myristate, lanolin alcohols, magnesium stearate, mineral oil, paraffin wax, purified water, and white petrolatum.

The chemical name of desoximetasone is Pregna-1,4-diene-3,20-dione,9-fluoro-11,21-dihydroxy-16-methyl-,(11β,16α)-. Desoximetasone has the molecular formula C22H29FO4 and a molecular weight of 376.47. The CAS Registry Number is 382-67-2. The chemical structure is:

CLINICAL PHARMACOLOGY

Topical corticosteroids share anti-inflammatory, anti-pruritic and vasoconstrictive actions. The mechanism of anti-inflammatory activity of the topical corticosteroids is unclear. Various laboratory methods, including vasoconstrictor assays, are used to compare and predict potencies and/or clinical efficacies of the topical corticosteroids. There is some evidence to suggest that a recognizable correlation exists between vasoconstrictor potency and therapeutic efficacy in man.

Pharmacokinetics -

The extent of percutaneous absorption of topical corticosteroids is determined by many factors including the vehicle, the integrity of the epidermal barrier, and the use of occlusive dressings.

Topical corticosteroids can be absorbed from normal intact skin. Inflammation and/or other disease processes in the skin increase percutaneous absorption. Occlusive dressings substantially increase the percutaneous absorption of topical corticosteroids. Thus, occlusive dressings may be a valuable therapeutic adjunct for treatment of resistant dermatoses.

Once absorbed through the skin, topical corticosteroids are handled through pharmacokinetic pathways similar to systemically administered corticosteroids. Corticosteroids are bound to plasma proteins in varying degrees. Corticosteroids are metabolized primarily in the liver and are then excreted by the kidneys. Some of the topical corticosteroids and their metabolites are also excreted into the bile.

Pharmacokinetic studies in men with desoximetasone cream 0.25% with tagged desoximetasone showed a total of 5.2% ± 2.9% excretion in urine (4.1% ± 2.3%) and feces (1.1% ± 0.6%) and no detectable level (limit of sensitivity: 0.005 µg/mL) in the blood when it was applied topically on the back followed by occlusion for 24 hours. Seven days after application, no further radioactivity was detected in urine or feces. The half-life of the material was 15 ± 2 hours (for urine) and 17 ± 2 hours (for feces) between the third and fifth trial day. Studies with other similarly structured steroids have shown that predominant metabolite reaction occurs through conjugation to form the glucuronide and sulfate ester.

INDICATIONS AND USAGE

Desoximetasone Cream USP, 0.25% is indicated for the relief of the inflammatory and pruritic manifestations of corticosteroid-responsive dermatoses.

CONTRAINDICATIONS

Topical corticosteroids are contraindicated in those patients with a history of hypersensitivity to any of the components of the preparation.

WARNINGS

Desoximetasone Cream USP, 0.25% is not for ophthalmic use.

Keep out of reach of children.

PRECAUTIONS

General -

Systemic absorption of topical corticosteroids has produced reversible hypothalamic-pituitary-adrenal (HPA) axis suppression, manifestations of Cushing's syndrome, hyperglycemia, and glucosuria in some patients. Conditions which augment systemic absorption include the application of the more potent steroids, use over large surface areas, prolonged use, and the addition of occlusive dressings.

Therefore, patients receiving a large dose of a potent topical steroid applied to a large surface area or under an occlusive dressing should be evaluated periodically for evidence of HPA axis suppression by using the urinary free cortisol and ACTH stimulation tests. If HPA axis suppression is noted, an attempt should be made to withdraw the drug, to reduce the frequency of application, or to substitute a less potent steroid. Recovery of HPA axis function is generally prompt and complete upon discontinuation of the drug. Infrequently, signs and symptoms of steroid withdrawal may occur, requiring supplemental systemic corticosteroids.

Pediatric patients may absorb proportionally larger amounts of topical corticosteroids and thus be more susceptible to systemic toxicity. (See PRECAUTIONS – Pediatric Use). If irritation develops, topical corticosteroids should be discontinued and appropriate therapy instituted.

In the presence of dermatological infections, the use of an appropriate antifungal or antibacterial agent should be instituted. If a favorable response does not occur promptly, the corticosteroid should be discontinued until the infection has been adequately controlled.

Information for Patients

Patients using topical corticosteroids should receive the following information and instructions:

1. This medication is to be used as directed by the physician. It is for external use only. Avoid contact with the eyes.
2. Patients should be advised not to use this medication for any disorder other than for which it was prescribed.
3. The treated skin area should not be bandaged or otherwise covered or wrapped as to be occlusive unless directed by the physician.
4. Patients should report any signs of local adverse reactions, especially under occlusive dressing.
5. Parents of pediatric patients should be advised not to use tight-fitting diapers or plastic pants on a child being treated in the diaper area, as these garments may constitute occlusive dressings.

Laboratory Tests

The following tests may be helpful in evaluating the HPA axis suppression:

Urinary free cortisol test

ACTH stimulation test

Carcinogenesis, Mutagenesis, Impairment of Fertility -

Long-term animal studies have not been performed to evaluate the carcinogenic potential or the effect on fertility of topical corticosteroids.

Studies to determine mutagenicity with prednisolone and hydrocortisone have revealed negative results. Desoximetasone did not show potential for mutagenic activity in vitro in the Ames microbial mutagen test with or without metabolic activation.

Pregnancy:

Teratogenic Effects:

Pregnancy Category C -

Corticosteroids are generally teratogenic in laboratory animals when administered systemically at relatively low dosage levels. The more potent corticosteroids have been shown to be teratogenic after dermal application in laboratory animals.

Desoximetasone has been shown to be teratogenic and embryotoxic in mice, rats, and rabbits when given by subcutaneous or dermal routes of administration in doses 3 to 30 times the human dose of Desoximetasone Cream USP, 0.25%.

There are no adequate and well-controlled studies in pregnant women on teratogenic effects from topically applied corticosteroids. Therefore, Desoximetasone Cream USP, 0.25% should be used during pregnancy only if the potential benefit justifies the potential risk to the fetus. Drugs of this class should not be used extensively on pregnant patients, in large amounts, or for prolonged periods of time.

Nursing Mothers -

It is not known whether topical administration of corticosteroids could result in sufficient systemic absorption to produce detectable quantities in breast milk. Systemically administered corticosteroids are secreted into breast milk in quantities not likely to have a deleterious effect on the infant. Nevertheless, caution should be exercised when topical corticosteroids are administered to a nursing woman.

Pediatric Use -

Pediatric patients may demonstrate greater susceptibility to topical corticosteroid-induced HPA axis suppression and Cushing's syndrome than mature patients because of a larger skin surface area to body weight ratio. HPA axis suppression, Cushing's syndrome, and intracranial hypertension have been reported in pediatric patients receiving topical corticosteroids. Manifestations of adrenal suppression in pediatric patients include linear growth retardation, delayed weight gain, low plasma cortisol levels, and absence of response to ACTH stimulation. Manifestations of intracranial hypertension include bulging fontanelles, headaches, and bilateral papilledema.

Administration of topical corticosteroids to pediatric patients should be limited to the least amount compatible with an effective therapeutic regimen. Chronic corticosteroid therapy may interfere with the growth and development of pediatric patients.

ADVERSE REACTIONS

The following local adverse reactions are reported infrequently with topical corticosteroids, but may occur more frequently with the use of occlusive dressings. These reactions are listed in an approximate decreasing order of occurrence: burning, itching, irritation, dryness, folliculitis, hypertrichosis, acneiform eruptions, hypopigmentation, perioral dermatitis, allergic contact dermatitis, maceration of the skin, secondary infection, skin atrophy, striae, miliaria

In controlled clinical studies, the incidence of adverse reactions was low (0.8%) for desoximetasone cream 0.25%, and included burning, folliculitis and folliculo-pustular lesions.

OVERDOSAGE

Topically applied corticosteroids can be absorbed in sufficient amounts to produce systemic effects (see PRECAUTIONS).

DOSAGE AND ADMINISTRATION

Apply a thin film of Desoximetasone Cream USP, 0.25% to the affected skin areas twice daily. Rub in gently.

HOW SUPPLIED

Desoximetasone Cream USP, 0.25% is available as follows:

- NDC 72162-2330-2: 15 g in a TUBE

Repackaged/Relabeled by:
Bryant Ranch Prepack, Inc.
Burbank, CA 91504

STORAGE

Store at 20-25°C (68-77°F) [see USP Controlled Room Temperature].

Manufactured By

Perrigo plc

Bronx, NY 10457

Distributed By

PadagisTM

Allegan, MI 49010 ∙ www.padagis.com

Rev 01-22

2C500 RC JX2

PACKAGE LABEL

Desoximetasone 0.25% Cream

Extended Label